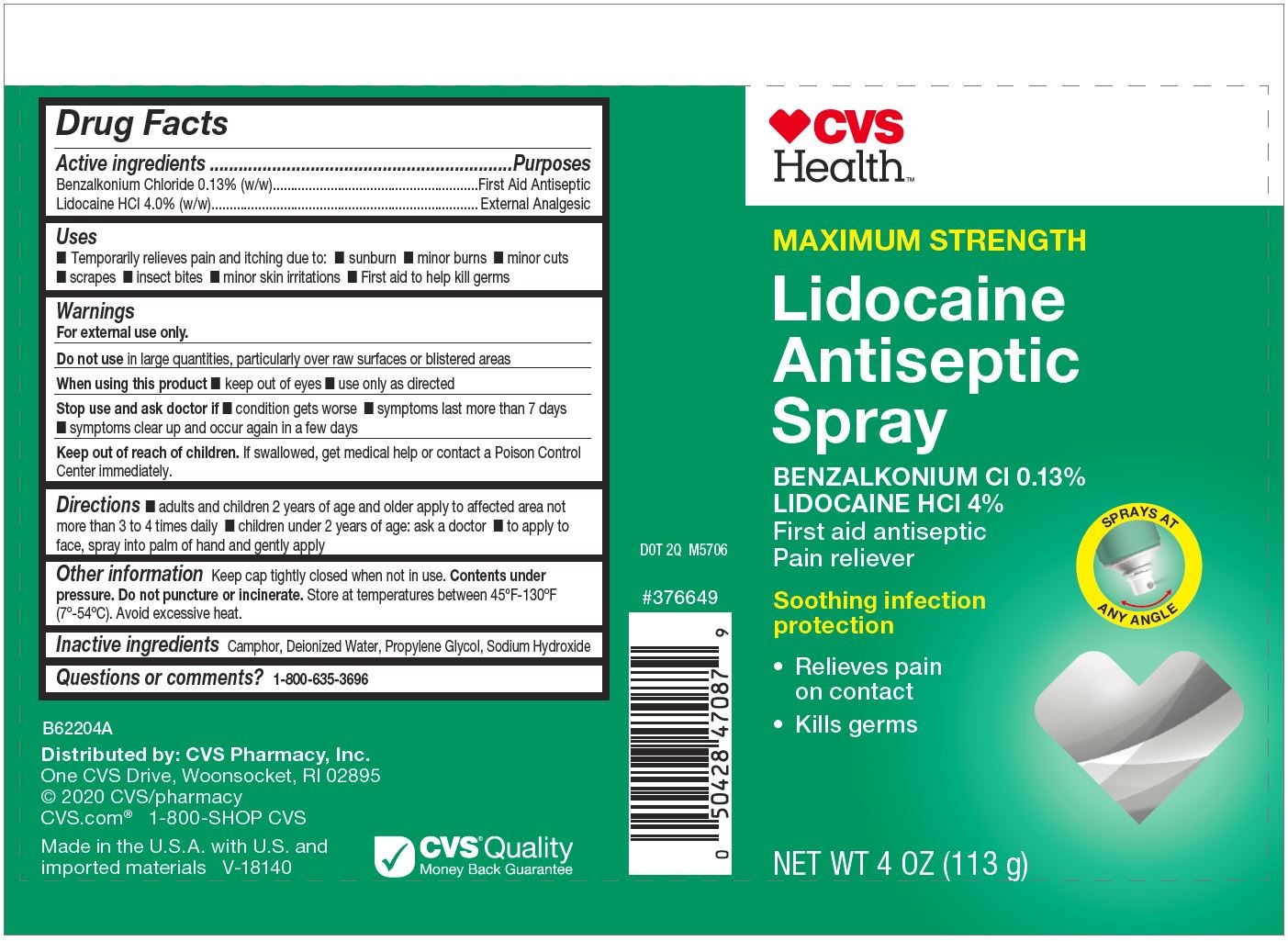 DRUG LABEL: CVSLidocaineAntisepticSpray
NDC: 69842-710 | Form: SPRAY
Manufacturer: CVS Health
Category: otc | Type: HUMAN OTC DRUG LABEL
Date: 20220113

ACTIVE INGREDIENTS: BENZALKONIUM CHLORIDE 0.013 g/1 g; LIDOCAINE 0.04 g/1 g
INACTIVE INGREDIENTS: PROPYLENE GLYCOL; CAMPHOR (SYNTHETIC); WATER; SODIUM HYDROXIDE

CVS Lidocaine Antiseptic Spray

PURPOSE

Temporarily relieves pain and itching due to: sunburn,minor burns,minor cuts,scrapes, insect bites,minor skin irritations,First aid to help kill germs.

Drug Facts

Active ingredients

Active ingredients | Purposes
Benzalkonium Chloride 0.13% (w/w) | First Aid Antiseptic
Lidocaine HCl 4.0% (w/w) | External Analgesic

Uses

■ Temporarily relieves pain and itching due to: ■ sunburn ■ minor burns ■ minor cuts
■ scrapes ■ insect bites ■ minor skin irritations ■ First aid to help kill germs

Warnings

For external use only.

Do not use in large quantities, particularly over raw surfaces or blistered areas

When using this product ■ keep out of eyes ■ use only as directed

Stop use and ask doctor if ■ condition gets worse ■ symptoms last more than 7 days
■ symptoms clear up and occur again in a few days

Keep out of reach of children. If swallowed, get medical help or contact a Poison Control
Center immediately.

Directions

■ adults and children 2 years of age and older apply to affected area not more than 3 to 4 times daily ■ children under 2 years of age: ask a doctor ■ to apply to face, spray into palm of hand and gently apply

Other information

Keep cap tightly closed when not in use. Contents under pressure. Do not puncture or incinerate. Store at temperatures between 45ºF-130ºF (7º-54ºC). Avoid excessive heat.

Inactive ingredients

Camphor, Deionized Water, Propylene Glycol, Sodium Hydroxide

Questions or comments?

1-800-635-3696

Principal Display Panel

CVS

Health™

MAXIMUM STRENGTH

Lidocaine
Antiseptic
Spray

BENZALKONIUM Cl 0.13%
LIDOCAINE HCl 4%

First aid antiseptic
Pain reliever

SPRAYS

ANY ANGLE

Soothing infection
protection

- Relieves pain

on contact

- Kills germs

NET WT 4 OZ (113 g)